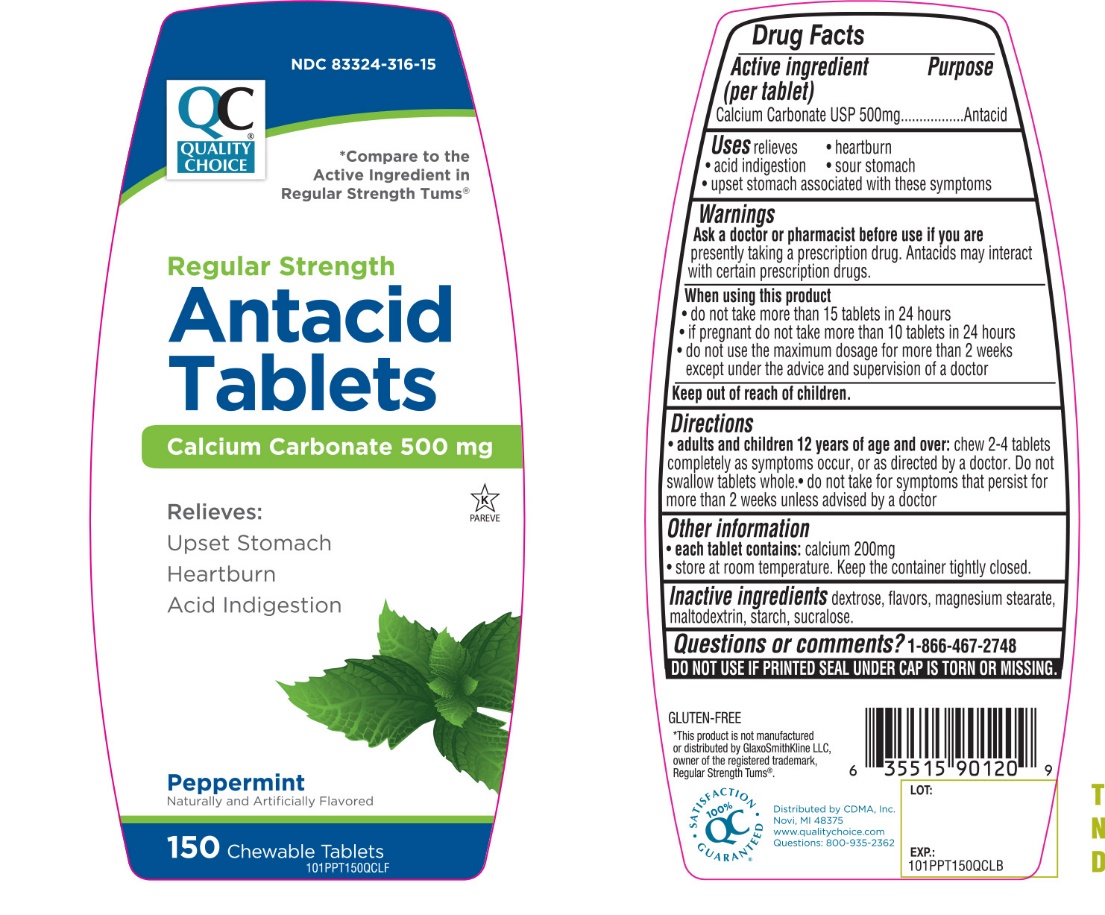 DRUG LABEL: QUALITY CHOICE

NDC: 83324-316 | Form: TABLET, CHEWABLE
Manufacturer: QUALITY CHOICE (Chain drug Marketing Assoiciation)
Category: otc | Type: HUMAN OTC DRUG LABEL
Date: 20251204

ACTIVE INGREDIENTS: CALCIUM CARBONATE 500 mg/1 1
INACTIVE INGREDIENTS: DEXTROSE, UNSPECIFIED FORM; MAGNESIUM STEARATE; MALTODEXTRIN; STARCH, CORN; SUCRALOSE

Quality Choice Regular Strength Peppermint Flavor Antacid Drug Facts

Active ingredient (per tablet)

Calcium Carbonate USP 500mg

Purpose

Antacid

Uses

relieves

- heartburn
- acid indigestion
- sour stomach
- upset stomach associated with these symptoms

Warnings

Ask a doctor or pharmacist before use if you are

presently taking a prescription drug. Antacids may interact with certain prescription drugs.

When using this product

- do not take more than 15 tablets in 24 hours
- if pregnant do not take more than 10 tablets in 24 hours
- do not use the maximum dosage for more than 2 weeks except under the advice and supervision of a doctor

Directions

- adults and children 12 years of age and over:chew 2-4 tablets completely as symptoms occur, or as directed by a doctor. Do not swallow tablets whole.
- do not take for symptoms that persist for more than 2 weeks unless advised by a doctor

Other information

- each tablet contains: calcium 200mg
- store at room temperature. Keep the container tightly closed.

Inactive ingredients

dextrose, flavor, magnesium stearate, maltodextrin, starch, sucralose.

Questions or comments?

1-866-467-2748

SAFETY SEALED:DO NOT USE IF PRINTED SEAL UNDER CAP IS TORN OR MISSING.

Principal Display Panel

*Compare to the Active Ingredient in Regular Strength Tums®

NDC#83324-316-15

Regular Strength

Antacid Tablets

Calcium Carbonate 500 mg

Relieves:

- Upset Stomach
- Heartburn
- Acid Indigestion

Peppermint

Naturally and Artificially Flavored

100% QC SATISFACTION GUARANTEED

GLUTEN FREE

150 CHEWABLE TABLETS

K PAREVE

Distributed By:

C.D.M.A. Inc.

Novi, MI 48375

www.qualitychoice.com

Questions: 800-935-2362

*This product is not manufactured or distributed by GlaxoSmithKline LLC, owner of the registered trademark, Regular Strength Tums®.